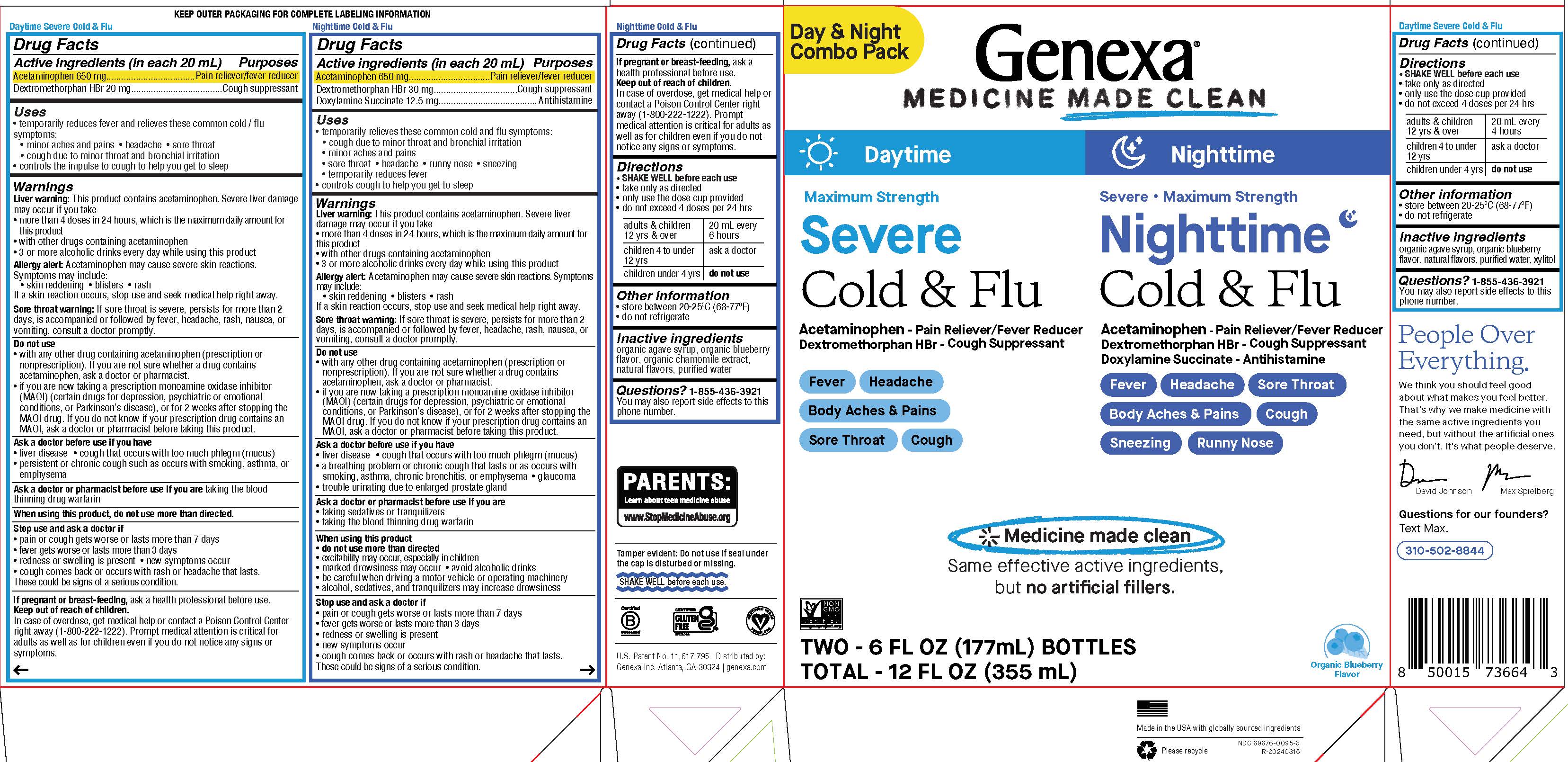 DRUG LABEL: Daytime and Nighttime Severe Cold and Flu combo pack
NDC: 69676-0095 | Form: KIT | Route: ORAL
Manufacturer: Genexa Inc.
Category: otc | Type: HUMAN OTC DRUG LABEL
Date: 20251230

ACTIVE INGREDIENTS: ACETAMINOPHEN 650 mg/20 mL; DEXTROMETHORPHAN HYDROBROMIDE 20 mg/20 mL; DEXTROMETHORPHAN HYDROBROMIDE 30 mg/20 mL; ACETAMINOPHEN 650 mg/20 mL; DOXYLAMINE SUCCINATE 12.5 mg/20 mL
INACTIVE INGREDIENTS: AGAVE TEQUILANA JUICE; WATER; XYLITOL; BLUEBERRY; AGAVE TEQUILANA JUICE; WATER; BLUEBERRY; CHAMOMILE

Daytime and Nighttime Severe Cold & Flu Combo pack

Daytime Severe Cold & Flu

Drug Facts

Active ingredients (in each 20 mL)

Acetaminophen 650 mg

Dextromethorphan HBr 20 mg

Purposes

Pain reliever/fever reducer

Cough suppressant

Uses

- temporarily reduces fever and relieves these common cold/flu symptoms:
- minor aches and pains
- headache
- sore throat
- cough due to minor throat and bronchial irritation

- controls the impulse to cough to help you get to sleep

Warnings

Liver warning: This product contains acetaminophen. Severe liver damage may occur if you take

- more than 4 doses in 24 hours, which is the maximum daily amount for this product
- with other drugs containing acetaminophen
- 3 or more alcoholic drinks every day while using this product

Allergy alert: Acetaminophen may cause severe skin reactions.

Symptoms may include:

- skin reddening
- blisters
- rash

If a skin reaction occurs, stop use and seek medical help right away.

Sore throat warning: If sore throat is severe, persists for more than 2 days, is accompanied or followed by fever, headache, rash, nausea, or vomiting, consult a doctor promptly.

Do not use

- with any other drug containing acetaminophen (prescription or nonprescription). If you are not sure whether a drug contains acetaminophen, ask a doctor or pharmacist.
- if you are now taking a prescription monoamine oxidase inhibitor (MAOI) (certain drugs for depression, psychiatric or emotional conditions, or Parkinson's disease), or for 2 weeks after stopping the MAOI drug. If you do not know if your prescription drug contains an MAOI, ask a doctor or pharmacist before taking this product.

Ask a doctor before use if you have

- liver disease
- cough that occurs with too much phlegm (mucus)
- persistent or chronic cough such as occurs with smoking, asthma, or emphysema

Ask a doctor or pharmacist before use if you are taking the blood thinning drug warfarin

When using this product, do not use more than directed.

Stop use and ask a doctor if

- pain or cough gets worse or lasts more than 7 days
- fever gets worse or lasts more than 3 days
- redness or swelling is present
- new symptoms occur
- cough comes back or occurs with rash or headache that lasts.

These could be signs of a serious condition.

PREGNANCY OR BREAST FEEDING

If pregnant or breast-feeding, ask a health professional before use.

Keep out of reach of children.

In case of overdose, get medical help or contact a Poison Control Center right away (1-800-222-1222). Prompt medical attention is critical for adults as well as for children even if you do not notice any signs or symptoms.

Directions

- SHAKE WELL before each use
- take only as directed
- only use the dose cup provided
- do not exceed 4 doses per 24 hrs

adults & children 12 yrs & over | 20 mL every 4 hours
children 4 to under 12 yrs | ask a doctor
children under 4 yrs | do not use

Other information

- store between 20-25°C (68-77°F)
- do not refrigerate

Inactive ingredients

organic agave syrup, organic blueberry flavor, natural flavors, purified water, xylitol

Questions? 1-855-436-3921

You may also report side effects to this phone number.

Nighttime Severe Cold & Flu

Drug Facts

Active ingredients (in each 20 mL)

Acetaminophen 650 mg

Dextromethorphan HBr 30 mg

Doxylamine Succinate 12.5 mg

Purposes

Pain reliever/fever reducer

Cough suppressant

Antihistamine

Uses

- temporarily relieves these common cold and flu symptoms:
- cough due to minor throat and bronchial irritation
- minor aches and pains
- sore throat
- headache
- runny nose
- sneezing
- temporarily reduces fever

- controls cough to help you get to sleep

Warnings

Liver warning: This product contains acetaminophen. Severe liver damage may occur if you take

- more than 4 doses in 24 hours, which is the maximum daily amount for this product
- with other drugs containing acetaminophen
- 3 or more alcoholic drinks every day while using this product

Allergy alert: Acetaminophen may cause severe skin reactions.

Symptoms may include:

- skin reddening
- blisters
- rash

If a skin reaction occurs, stop use and seek medical help right away.

Sore throat warning: If sore throat is severe, persists for more than 2 days, is accompanied or followed by fever, headache, rash, nausea, or vomiting, consult a doctor promptly.

Do not use

- with any other drug containing acetaminophen (prescription or nonprescription). If you are not sure whether a drug contains acetaminophen, ask a doctor or pharmacist.
- if you are now taking a prescription monoamine oxidase inhibitor (MAOI) (certain drugs for depression, psychiatric or emotional conditions, or Parkinson's disease), or for 2 weeks after stopping the MAOI drug. If you do not know if your prescription drug contains an MAOI, ask a doctor or pharmacist before taking this product.

Ask a doctor before use if you have

- liver disease
- cough that occurs with too much phlegm (mucus)
- a breathing problem or chronic cough that lasts or as occurs with smoking, asthma, chronic bronchitis, or emphysema
- glaucoma
- trouble urinating due to enlarged prostate gland

Ask a doctor or pharmacist before use if you are

- taking sedatives or tranquilizers
- taking the blood thinning drug warfarin

When using this product

- do not use more than directed
- excitability may occur, especially in children
- marked drowsiness may occur
- avoid alcoholic drinks
- be careful when driving a motor vehicle or operating machinery
- alcohol, sedatives, and tranquilizers may increase drowsiness

Stop use and ask a doctor if

- pain or cough gets worse or lasts more than 7 days
- fever gets worse or lasts more than 3 days
- redness or swelling is present
- new symptoms occur
- cough comes back or occurs with rash or headache that lasts.

These could be signs of a serious condition.

PREGNANCY OR BREAST FEEDING

If pregnant or breast-feeding, ask a health professional before use.

Keep out of reach of children.

In case of overdose, get medical help or contact Poison Control Center right away (1-800-222-1222). Prompt medical attention is critical for adults as well as for children even if you do not notice any signs or symptoms.

Directions

- SHAKE WELL before each use
- take only as directed
- only use the dose cup provided
- do not exceed 4 doses per 24 hours

adults & children 12 yrs & over | 20 mL every 6 hours
children 4 to under 12 yrs | ask a doctor
children under 4 yrs | do not use

Other information

- store between 20-25°C (68-77°F)
- do not refrigerate

Inactive ingredients

organic agave syrup, organic blueberry flavor, organic chamomile extract, natural flavors, purified water

Questions? 1-855-426-3921

You may also report side effects to this phone number.

Tamper evident: Do not use if seal under the cap is disturbed or missing.

SHAKE WELL before each use.

U.S. Patent No. 11,617,795 | Distributed by: Genexa Inc. Atlanta, GA 30324 | genexa.com

Made in the USA with globally sourced ingredients

NDC 69676-0095-3

PACKAGE LABEL

Day & Night Combo Pack

Genexa®

MEDICINE MADE CLEAN

Daytime

Maximum Strength

Severe Cold & Flu

Acetaminophen - Pain Reliever/Fever Reducer

Dextromethorphan HBr - Cough Suppressant

Fever

Headache

Body Aches & Pains

Sore Throat

Cough

Nighttime

Severe • Maximum Strength

Nighttime Cold & Flu

Acetaminophen - Pain Reliever/Fever Reducer

Dextromethorphan HBr - Cough Suppressant

Doxylamine Succinate - Antihistamine

Fever

Headache

Sore Throat

Body Aches & Pains

Cough

Sneezing

Runny Nose

Medicine made clean

Same effective active ingredients, but no artificial fillers.

TWO - 6 FL OZ (177 mL) BOTTLES

TOTAL - 12 FL OZ (355 mL)

Organic Blueberry Flavor